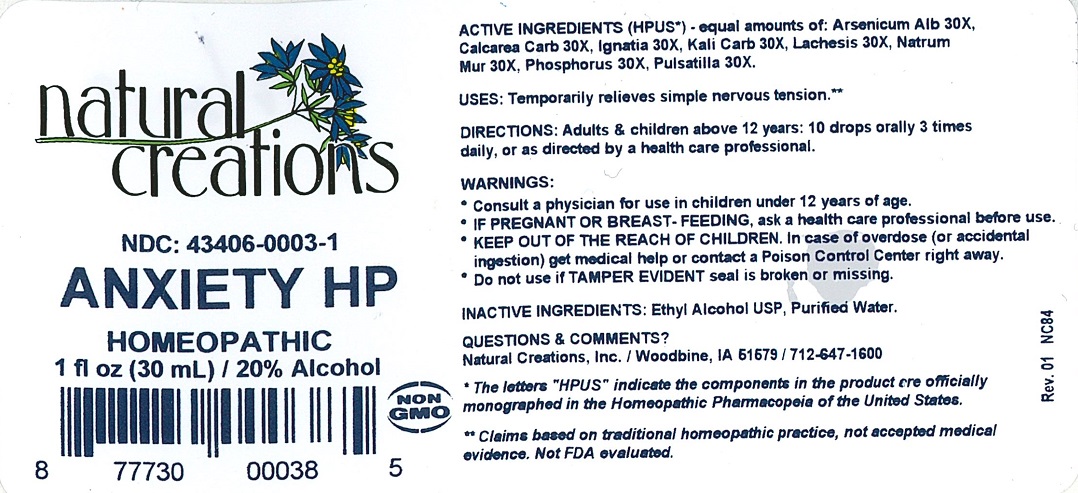 DRUG LABEL: Anxiety HP
NDC: 43406-0003 | Form: LIQUID
Manufacturer: Natural Creations, Inc.
Category: homeopathic | Type: HUMAN OTC DRUG LABEL
Date: 20251113

ACTIVE INGREDIENTS: ARSENIC TRIOXIDE 30 [hp_X]/1 mL; CALCIUM CARBONATE 30 [hp_X]/1 mL; STRYCHNOS IGNATII SEED 30 [hp_X]/1 mL; POTASSIUM CARBONATE 30 [hp_X]/1 mL; LACHESIS MUTA VENOM 30 [hp_X]/1 mL; SODIUM CHLORIDE 30 [hp_X]/1 mL; PHOSPHORUS 30 [hp_X]/1 mL; PULSATILLA VULGARIS 30 [hp_X]/1 mL
INACTIVE INGREDIENTS: ALCOHOL; WATER

Anxiety HP

ACTIVE INGREDIENT

Active Ingredients (HPUS*) - equal amounts of: Arsenicum Album 30X, Calcarea Carbonica 30X, Ignatia Amara 30X, Kali Carbonicum 30X, Lacheis Mutus 30X, Natrum Muriaticum 30X, Phosphorus 30X, Pulsatilla 30X

INDICATIONS AND USAGE

USES: Temporarily relieves simple nervous tension.**

WARNING:

- Consult a physician for use in children under 12 years of age.
- IF PREGNANT OR BREAST-FEEDING, ask a health care professional before use.
- KEEP OUT OF THE REACH OF CHILDREN. In case of overdose (or accidental ingestion) get medical help or contact a Poison Control Center right away.
- Do not use if TAMER EVIDENT seal is broken or missing.

DOSAGE AND ADMINISTRATION

DIRECTIONS: Adults and children above 12 years: 10 drops orally 3 times daily, or as directed by a health care professional.

REFERENCES

*The letters "HPUS" indicate the components in the product are officially monographed in the Homeopathic Pharmacopeia of the United States.

**Claims based on traditional homeopathic practice, not accepted medical evidence. Not FDA evaluated.

INACTIVE INGREDIENTS: Ethyl Alcohol USP, Purified Water.

QUESTIONS AND COMMENTS?

Natural Creations / Woodbine, IA 51579 / 712-647-1600

PURPOSE

USES: Temporarily relieves simple nervous tension.**

KEEP OUT OF REACH OF CHILDREN. In case of overdose (or accidental ingestion) get medical help or contact a Poison Control Center.

PACKAGE LABEL

NDC: 43406-0003-1

ANXIETY HP

HOMEOPATHIC

1 fl oz (30 mL) / 20% Alcohol

UPC: 877730000385 NON GMO Logo